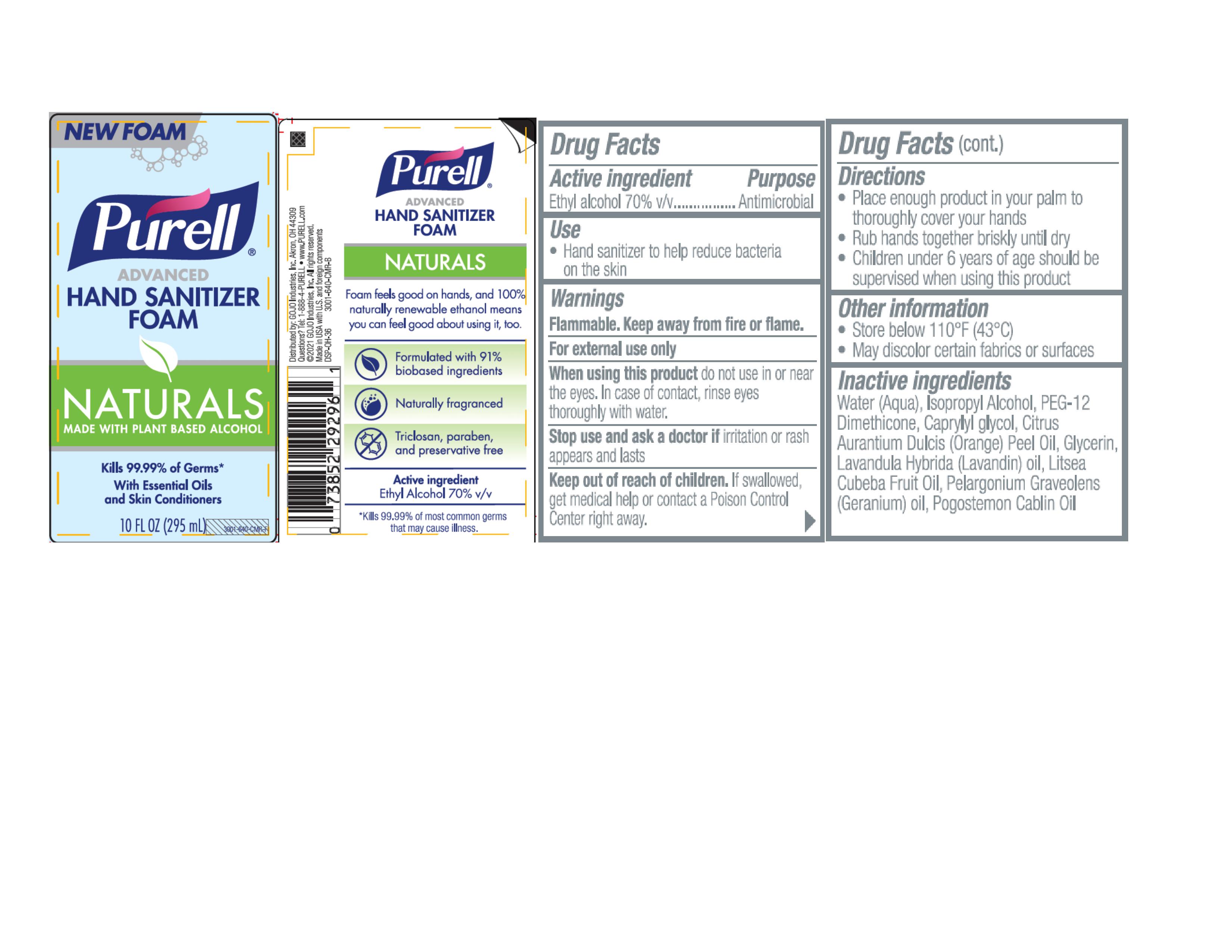 DRUG LABEL: PURELL Advanced Hand Sanitizer Naturals Foam
NDC: 21749-875 | Form: LIQUID
Manufacturer: GOJO Industries, Inc.
Category: otc | Type: HUMAN OTC DRUG LABEL
Date: 20241216

ACTIVE INGREDIENTS: ALCOHOL 70 mL/100 mL
INACTIVE INGREDIENTS: WATER; ISOPROPYL ALCOHOL; PEG-12 DIMETHICONE; CAPRYLYL GLYCOL; ORANGE OIL, COLD PRESSED; GLYCERIN; LAVANDIN OIL; LITSEA OIL; PELARGONIUM GRAVEOLENS FLOWER OIL; POGOSTEMON CABLIN LEAF OIL

PURELL Advanced Hand Sanitizer Naturals Foam

Active ingredient

Ethyl alcohol 70% v/v

Purpose

Antimicrobial

Uses

- Hand sanitizer to help reduce bacteria on the skin

Warnings

Flammable. Keep away from fire or flame.

For external use only

WHEN USING

When using this productdo not use in or near the eyes. In case of contact, rinse eyes thoroughly with water.

Stop use and ask a doctor ifirritation or rash appears and lasts

Keep out of reach of children.If swallowed, get medical help or contact a Poison Control Center right away.

Directions

- Place enough product in your palm to thoroughly cover your hands
- Run hands together briskly until dry
- Children under 6 years of age should be supervised when using this product

Inactive ingredients

Water (Aqua), Isopropyl Alcohol, PEG-12 Dimethicone, Caprylyl Glycol, Citrus Aurantium Dulcis (Orange) Peel Oil, Glycerin, Lavandula Hybrida (Lavandin) Oil, Litsea Cubeba Fruit Oil, Pelargonium Graveolens (Geranium) Oil, Pogostemon Cablin Oil